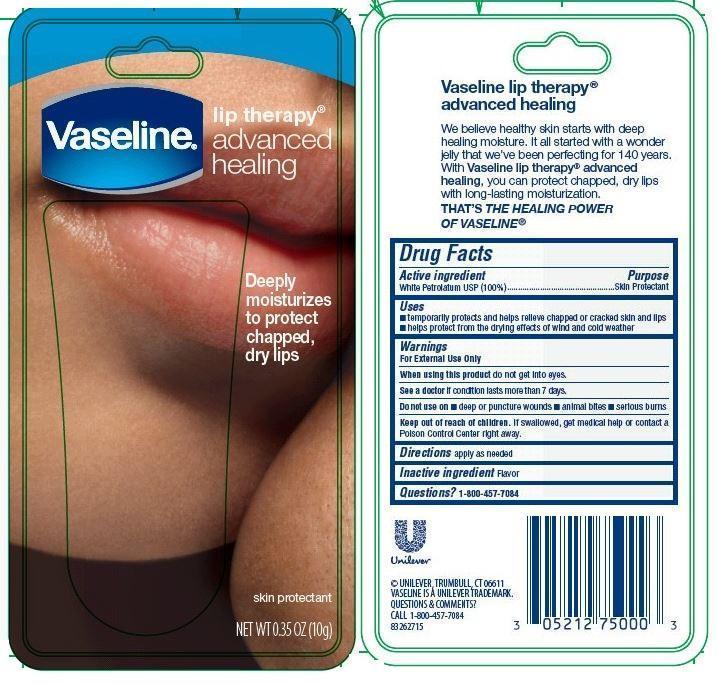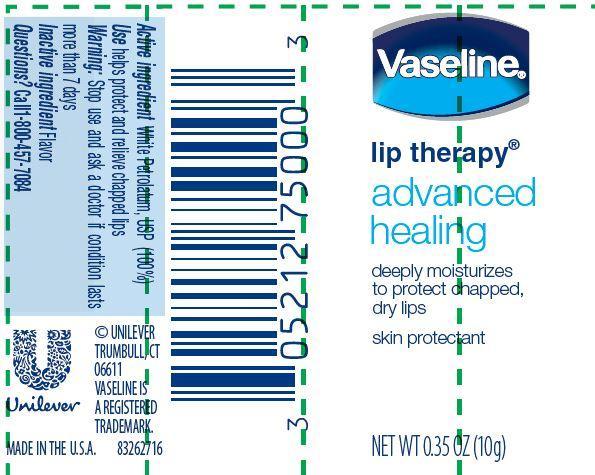 DRUG LABEL: Vaseline
NDC: 64942-1400 | Form: OINTMENT
Manufacturer: Conopco Inc. d/b/a Unilever
Category: otc | Type: HUMAN OTC DRUG LABEL
Date: 20221206

ACTIVE INGREDIENTS: PETROLATUM 100 g/100 g
INACTIVE INGREDIENTS: WATER

Vaseline Lip Therapy Advanced Healing

Drug Facts

Active ingredient

White Petrolatum, USP (100%)

Purpose

Skin Protectant

Uses

▪ temporarily protects and helps relieve chapped or cracked skin and lips
▪ helps protect from the drying effects of wind and cold weather

Warnings

For External Use Only

When using this product do not get into eyes.

ASK DOCTOR

See a doctor if condition lasts more than 7 days.

Do not use on ▪deep or puncture wounds ▪animal bites ▪serious burns

Keep out of reach of children. If swallowed get medical help or contact a Poison Control Center right away.

Directions

apply as needed

Inactive Ingredient

Flavor

Questions?

1-800-457-7084